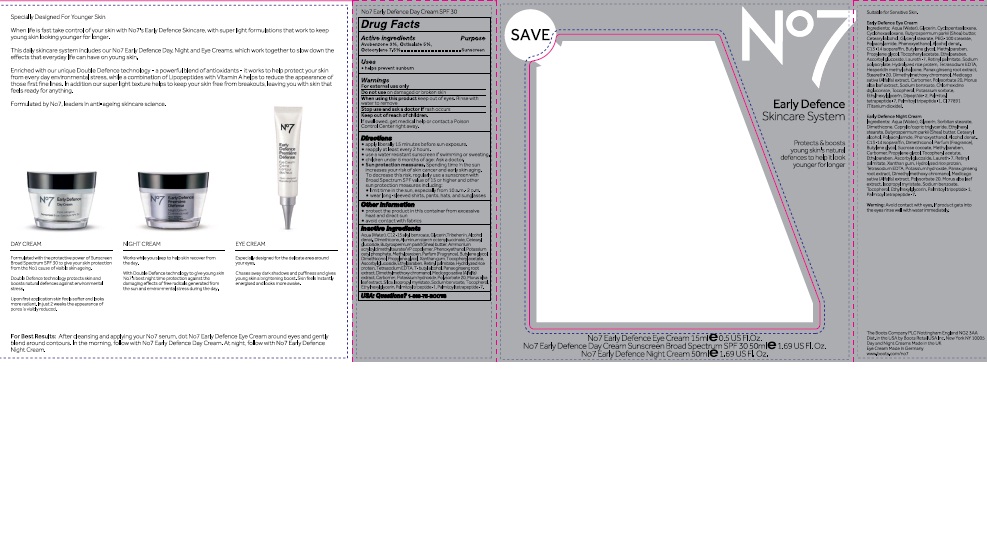 DRUG LABEL: No7 Early Defence Day Cream
NDC: 11489-102 | Form: CREAM
Manufacturer: BCM Ltd
Category: otc | Type: HUMAN OTC DRUG LABEL
Date: 20160922

ACTIVE INGREDIENTS: AVOBENZONE 1.5 g/1 g; OCTOCRYLENE 3.75 g/1 g; OCTISALATE 2.5 g/1 g
INACTIVE INGREDIENTS: WATER; GLYCERIN; ALUMINUM STARCH OCTENYLSUCCINATE; CETEARYL GLUCOSIDE; DIMETHICONE; TRIBEHENIN; AMMONIUM ACRYLOYLDIMETHYLTAURATE/VP COPOLYMER; PHENOXYETHANOL; SHEA BUTTER; POTASSIUM CETYL PHOSPHATE; BUTYLENE GLYCOL; DIMETHICONOL (100000 CST); PROPYLENE GLYCOL; METHYLPARABEN; ETHYLPARABEN; XANTHAN GUM; PANAX GINSENG ROOT OIL; VITAMIN A PALMITATE; ASCORBYL GLUCOSIDE; EDETATE SODIUM; TERT-BUTYL ALCOHOL; DIMETHYLMETHOXY CHROMANOL; POLYSORBATE 20; MEDICAGO SATIVA LEAF; POTASSIUM HYDROXIDE; CARBOMER 940; MORUS ALBA LEAF; ISOPROPYL MYRISTATE; SODIUM BENZOATE; ETHYLHEXYLGLYCERIN; TOCOPHEROL; PALMITOYL TRIPEPTIDE-1; PALMITOYL TETRAPEPTIDE-7

No7 Early Defence Day Cream Sunscreen Broad Spectrum SPF 30

Carton Active Ingredients Section

Active ingredients

Avobenzone 3%

Octisalate 5%

Octocrylene 7.5%

Uses

Uses - helps prevent sunburn

Warnings

For external use only

Do not use on damaged or broken skin

When using this product keep out of eyes. Rinse with water to remove.

Ask a doctor

Stop use and ask a doctor if rash occurs

Keep out of reach of children

If swallowed, get medical help or contact a Poison Control Center right away

Directions

Apply liberally 15 minutes before sun exposure

reapply at least every 2 hours

use a water resistant sunscreen if swimming or sweating

children under 6 months of age: Ask a doctor

Sun Protection Measures. Spending time in the sun increases your risk of skin cancer and early skin aging.

To decrease this risk, regularly use a sunscreen with a Broad Spectrum SPF value of 15 or higher and other sun protection measures including:

Limit time in the sun, especially from 10 a.m - 2 p.m.

wear long-sleeved shirts,pants,hats and sunglasses.

Storage

Other information

Protect the product in this container from excessive heat and direct sun

Avoid contact with fabrics

Inactive ingredients

Aqua(Water), Glycerin, C12-15 alkyl benzoate,Tribehenin, Alcohol denat, Dimethicone, Aluminum starch octenylsuccinate, Cetearyl glucoside, Butyrospermum parkii(Shea)butter, Ammonium acryloydimethyltaurate/VP copolymer, Phenoxyethanol, Potassium cetyl phosphate, Methylparaben, Parfum(Fragrance), Butylene glycol, Dimethiconol, Propylene glycol, Xanthan gum, Tocopheryl acetate, Ascorbyl glucoside, Ethylparaben, Retinyl palmitate, Hydrolyzed rice protein, Tetrasodium EDTA, T-butyl alcohol, Panax ginseng root extract, Dimethylmethoxy chromanol, Medicago sativa(Alfalfa) extract, Carbomer, Potassium hydroxide, Polysorbate 20, Morus alba leaf extract, Silica, Isopropyl myristate, Sodium benzoate, Tocopherol, Ethylhexylglycerin, Palmitoyl tripeptide-1, Palmitoyl tetrapeptide-7

Description

Specially Designed For Younger Skin

When life is fast take control of your skin with No7's Early Defence Skincare, with super light formulations that work to keep young skin looking younger for longer.

This daily skincare system includes our No7 Early Defence Day, Night and Eye Creams, which work together to slow down the effects that everyday life can have on young skin.

Enriched with our unique Double Defence technology - a powerful blend of antioxidants - it works to help protect your skin from every day environmental stress,while a combination of Lipopeptides with Vitamin A helps to reduce the appearance of those first fine lines. In addition our super light texture helps to keep your skin free from breakouts,leaving you with skin that feels ready for anything.

Formulated by No7, leaders in anti-ageing skincare science.

DAY CREAM

Formulated with the protective power of Sunscreen Broad Spectrum SPF 30 to give your skin protection from the No1 cause of visible skin ageing.

Double Defence technology protects skin and boosts natural defences against environmental stress.

Upon first application skin feels softer and looks more radiant. In just 2 weeks the appearance of pores is visibly reduced.

NIGHT CREAM

Works while you sleep to help skin recover from the day.

With Double Defence technology to give young skin No7's best night time protection against the damaging effects of free radicals generated from the sun and environmental stress during the day.

EYE CREAM

Especially designed for the delicate area around your eyes. Chases away dark shadows and puffiness and gives young skin a brightening boost. Skin feels instantly energised and looks more awake.

For Best Results: After cleansing and applying your No7 serum, dot No7 Early Defence Eye Cream around eyes and gently blend around contours. In the morning, follow with No7 Early Defence Day Cream. At night, follow with No7 Early Defence Night Cream.

PATIENT COUNSELING INFORMATION

The Boots Company PLC Nottingham England NG2 3AA

Dist. in the USA by Boots Retail USA Inc. New York NY 10005

Day and Night Creams Made in the UK

Eye Cream Made in Germany

www.boots.com/no7